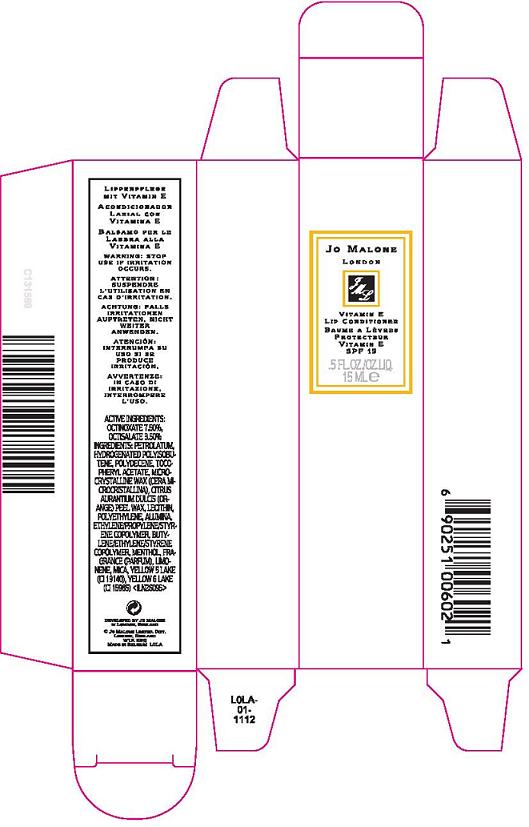 DRUG LABEL: VITAMIN E LIP CONDITIONER
NDC: 62874-995 | Form: CREAM
Manufacturer: JO MALONE LTD, Distr.
Category: otc | Type: HUMAN OTC DRUG LABEL
Date: 20100429

ACTIVE INGREDIENTS: OCTINOXATE 7.5 mL/100 mL; OCTISALATE 3.5 1/100 mL

ACTIVE INGREDIENTS: OCTINOXATE 7.5% [] OCTISALATE 3.5%

WARNINGS

WARNING: STOP USE IF IRRITATION OCCURS

PACKAGE LABEL

PRINCIPAL DISPLAY PANEL:

JO MALONE
LONDON
VITAMIN E LIP CONDITIONER
SPF 15
0.5 FL OZ LIQ/ 15 ML
DEVELOPED BY JO MALONE
IN LONDON, ENGLAND
JO MALONE LTD. DISTR.
LONDON, ENGLAND
W1K 3BQ